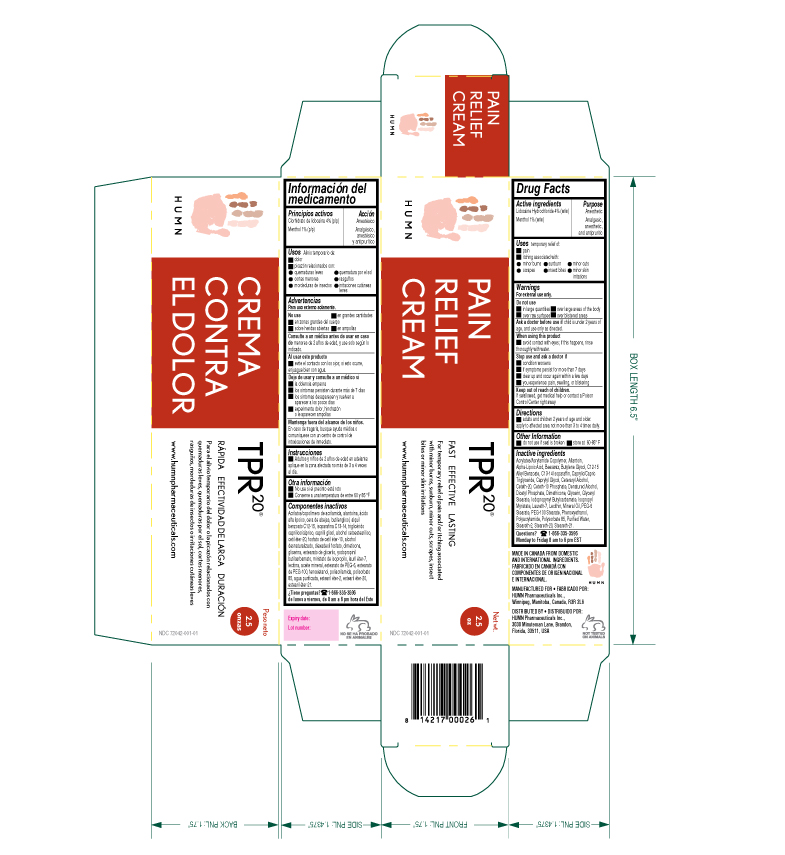 DRUG LABEL: Pain Relief
NDC: 72042-001 | Form: CREAM
Manufacturer: HUMN Pharmaceuticals Inc
Category: otc | Type: HUMAN OTC DRUG LABEL
Date: 20240117

ACTIVE INGREDIENTS: MENTHOL 1 mg/100 mg; LIDOCAINE HYDROCHLORIDE ANHYDROUS 4 mg/100 mg
INACTIVE INGREDIENTS: CETETH-20; ALCOHOL; ALUMINUM DICETYL PHOSPHATE; GLYCERIN; MINERAL OIL; PEG-6 STEARATE; PEG-100 STEARATE; POLYACRYLAMIDE (10000 MW); STEARETH-2; STEARETH-20; CETETH-10 PHOSPHATE; PEG-120 GLYCERYL STEARATE; IODOPROPYNYL BUTYLCARBAMATE; ISOPROPYL MYRISTATE; LAURETH-7; LECITHIN, SOYBEAN; PHENOXYETHANOL; DIMETHICONE 100; POLYSORBATE 85; WATER; CAPRYLYL GLYCOL; CAPRYLIC/CAPRIC/LAURIC TRIGLYCERIDE; C13-14 ISOPARAFFIN; ACRYLAMIDE; CETYL ALCOHOL; YELLOW WAX; BUTYLENE GLYCOL; ALKYL (C12-15) BENZOATE; ALLANTOIN; .ALPHA.-LIPOIC ACID; STEARETH-21

Pain Relief Cream TPR^20

Active ingredients

Lidocaine Hydrochloride 4.0% (w/w)

Menthol 1.0% (w/w)

Purpose

Anesthetic

Analgesic, anesthetic, and antipruritic

Uses

Temporary relief of:

• pain

• itching associated with:

▪ minor burns ▪ sunburn ▪ minor cuts ▪ scrapes ▪ insect bites ▪ minor skin irritations

Warnings

For external use only.

Do not use

• in large quantities • over large areas of the body • over raw surfaces • over blistered areas

Ask a doctor before use

if child is under 2 years of age, and use only as directed

When using this product

• avoid contact with eyes; if this happens, rinse thoroughly with water

Stop use and ask a doctor

• condition worsens • if symptoms persist for more than 7 days

• clear up and occur again within a few days • you experience: pain, swelling, or blistering

Keep out of reach of children. If swallowed, get

medical help or contact a Poison Control Center right away.

Directions

• adults and children 2 years of age and older: apply to affected area not more than 3 to 4 times daily.

Other information

• do not use if seal is broken

• store at 60-85° F

Inactive ingredients

Acrylates/Acrylamide Copolymer, Allantoin, Alpha-Lipoic Acid, Beeswax, Butylene Glycol, C12-15 Alkyl Benzoate, C13-14 Isoparaffin, Caprylic/Capric Triglyceride, Caprylyl Glycol, Ceteraryl Alcohol, Ceteth-20, Ceteth-10 Phosphate, Denatured Alcohol, Dicetyl Phosphate, Dimethicone, Glycerin, Glyceryl Stearate, Iodopropynyl Butylcarbamate, Isopropyl Myristate, Laureth-7, Lecithin, Mineral Oil, PEG-6 Stearate, PEG-100 Stearate, Phenoxyethanol, Polyacrylamide, Polysorbate 85, Purified Water, Steareth-2, Steareth-20, Steareth-21.

Questions?

1-866-335-3596 Monday to Friday 8 am to 6 pm EST .

TPR20 Pain Relief Label